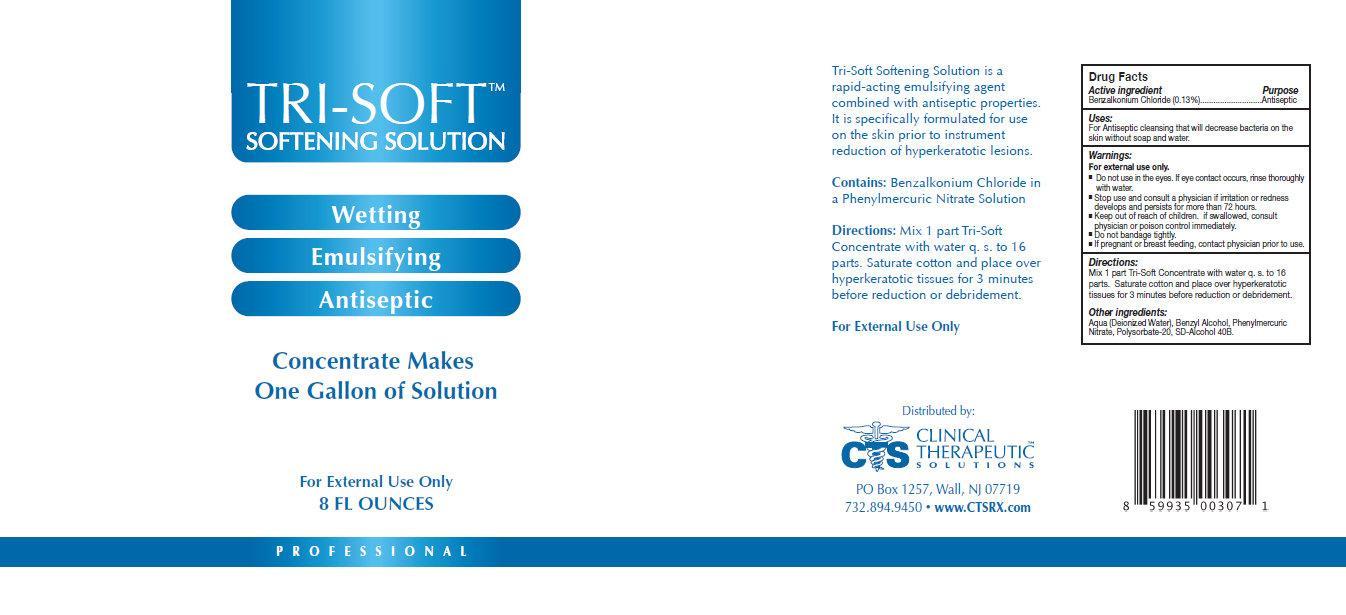 DRUG LABEL: TRI-SOFT SOFTENING
NDC: 44577-711 | Form: SOLUTION
Manufacturer: Clinical Therapeutic Solutions
Category: otc | Type: HUMAN OTC DRUG LABEL
Date: 20231105

ACTIVE INGREDIENTS: BENZALKONIUM CHLORIDE 1.3 mg/1 mL
INACTIVE INGREDIENTS: WATER; BENZYL ALCOHOL; PHENYLMERCURIC NITRATE; POLYSORBATE 20; ALCOHOL

TRI-SOFT SOFTENING SOLUTION

Active Ingredient

BENZALKONIUM CHLORIDE (0.13 %)

Purpose

Antiseptic

Uses:

For antiseptic cleansing that will decrease bacteria on the skin without soap and water.

Warnings

For external use only.

Do not use in the eyes. If eye contact occurs, rinse thoroughly with water.

Stop use and consult a physician if irritation or redness develops and persists for more than 72 hours.

Do not bandage tightly.

If pregnant or breast feeding, contact physician prior to use.

Keep out of reach of children

if swallowed, consult physician or poison control immediately

Directions

Mix 1 part Tri-Soft Concentrate with water q. s. to 16 parts. Saturate cotton and place over hyperkeratotic tissues for 3 minutes before reduction or debridement.

Other Ingredients

Aqua (Deionized Water), Benzyl Alcohol, Phenylmercuric Nitrate, Polysorbate-20, SD-Alcohol 40B.

Tri-Soft Softening Solution is a rapid-acting emulsifying agent combined with antiseptic properties.

It is specifically formulated for use on the skin prior to instrument reduction of hyperkeratotic lesions.